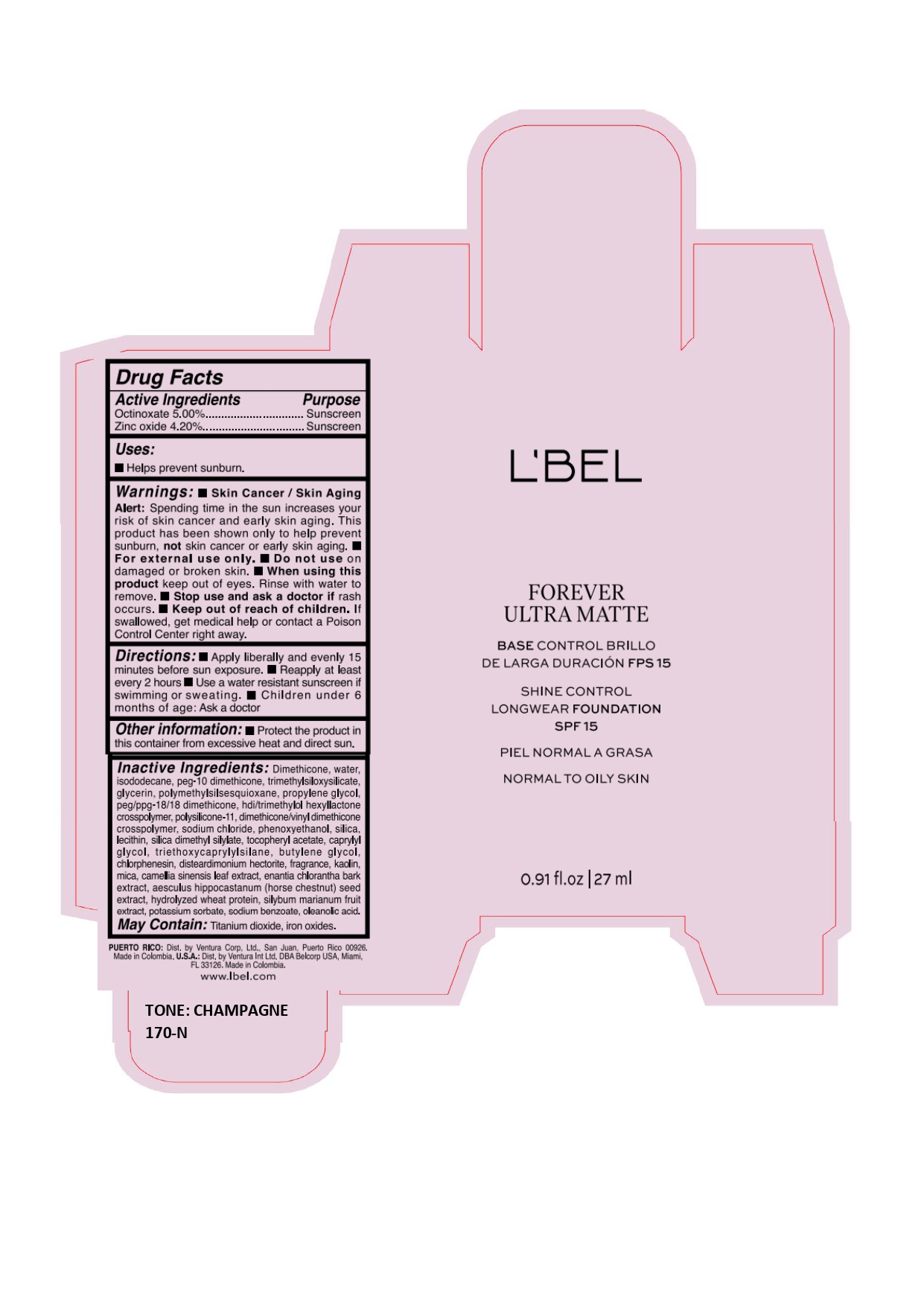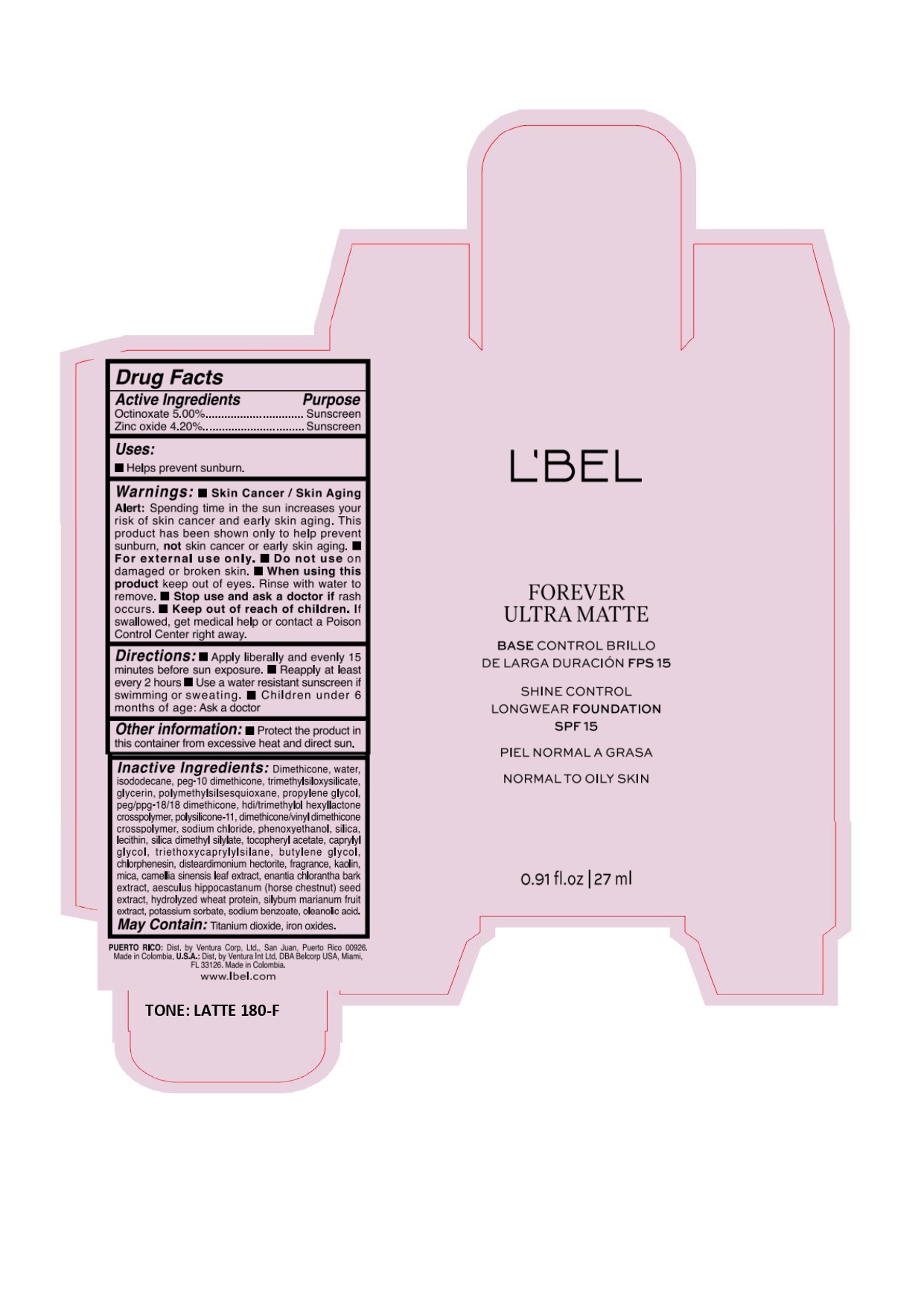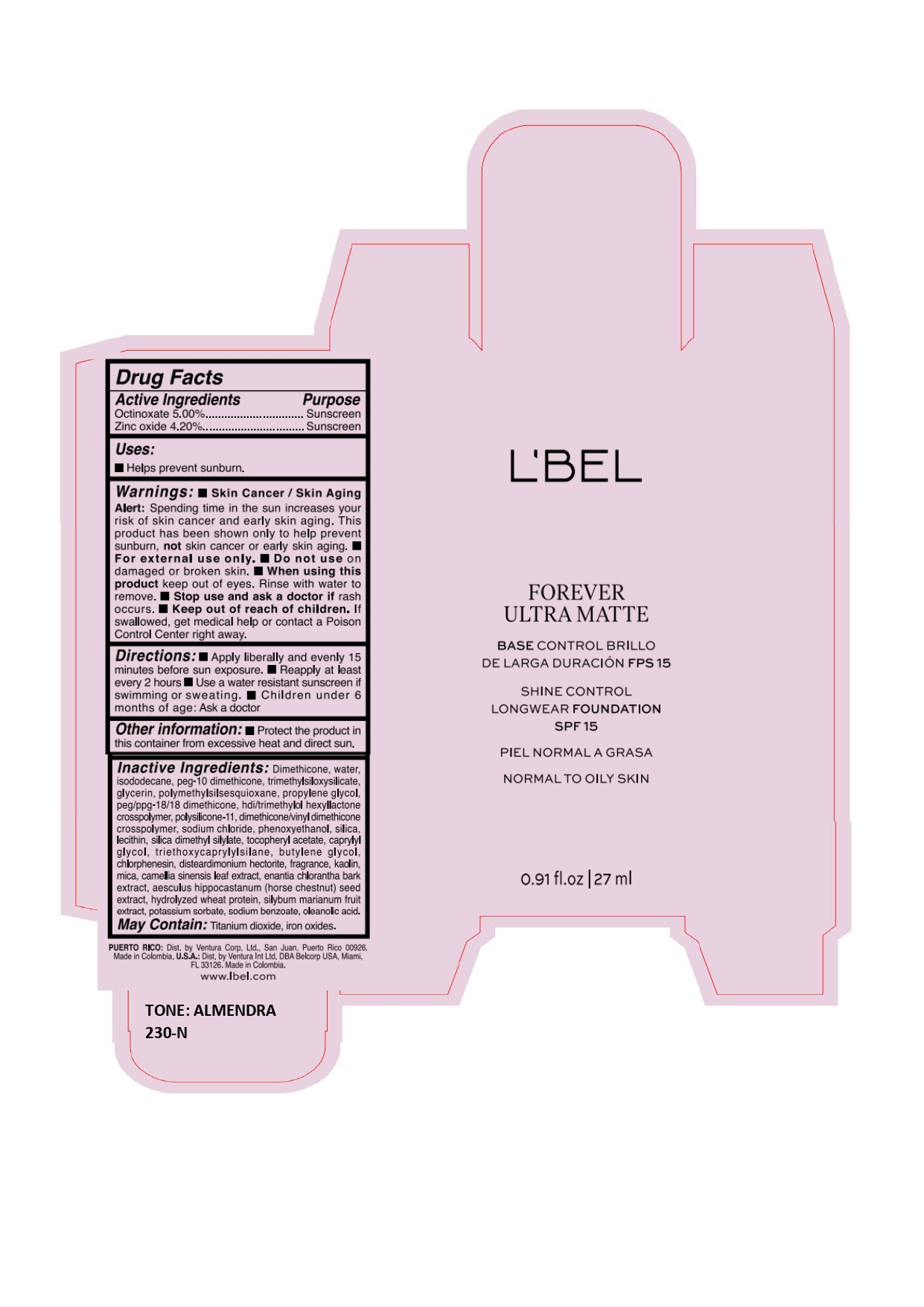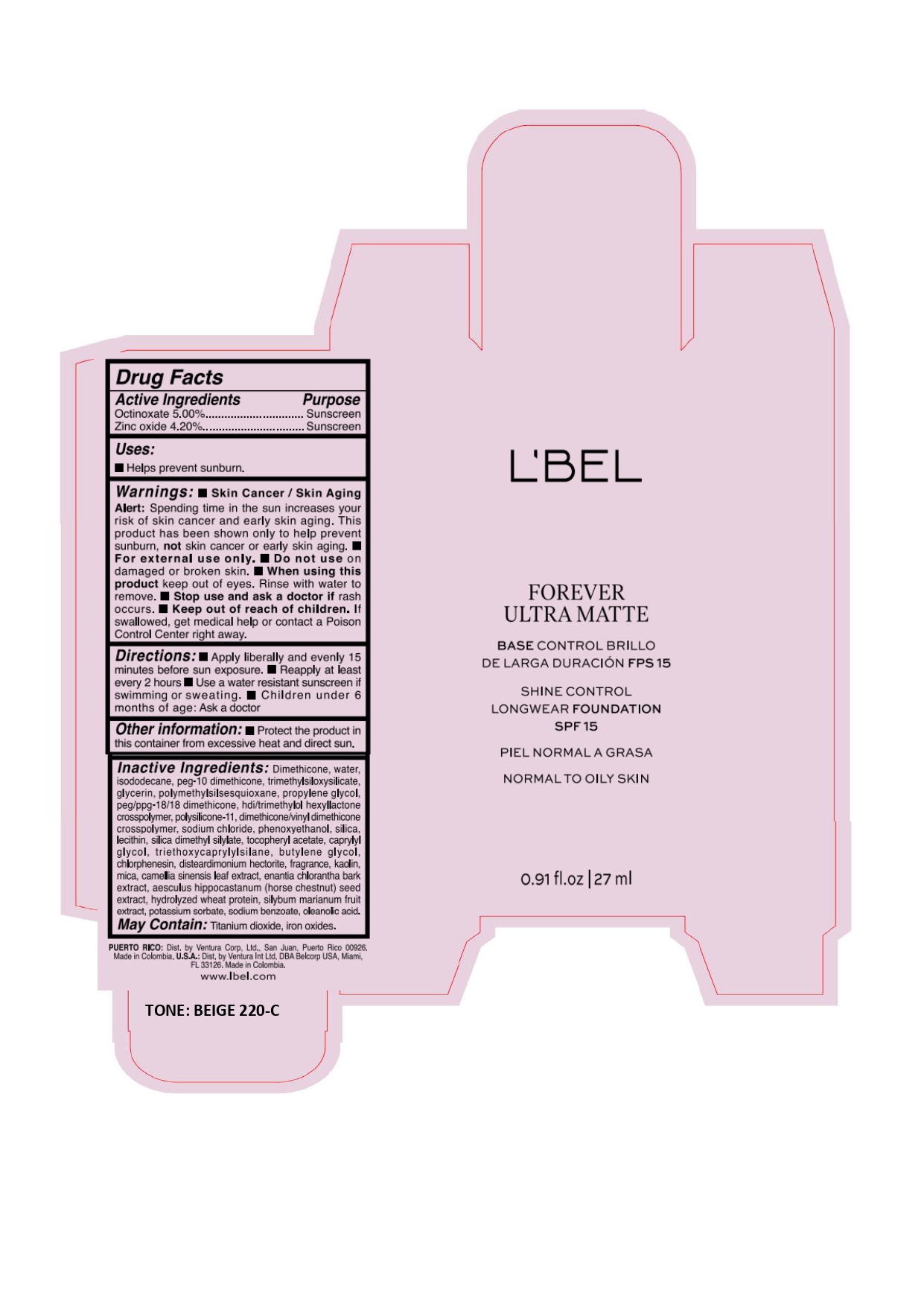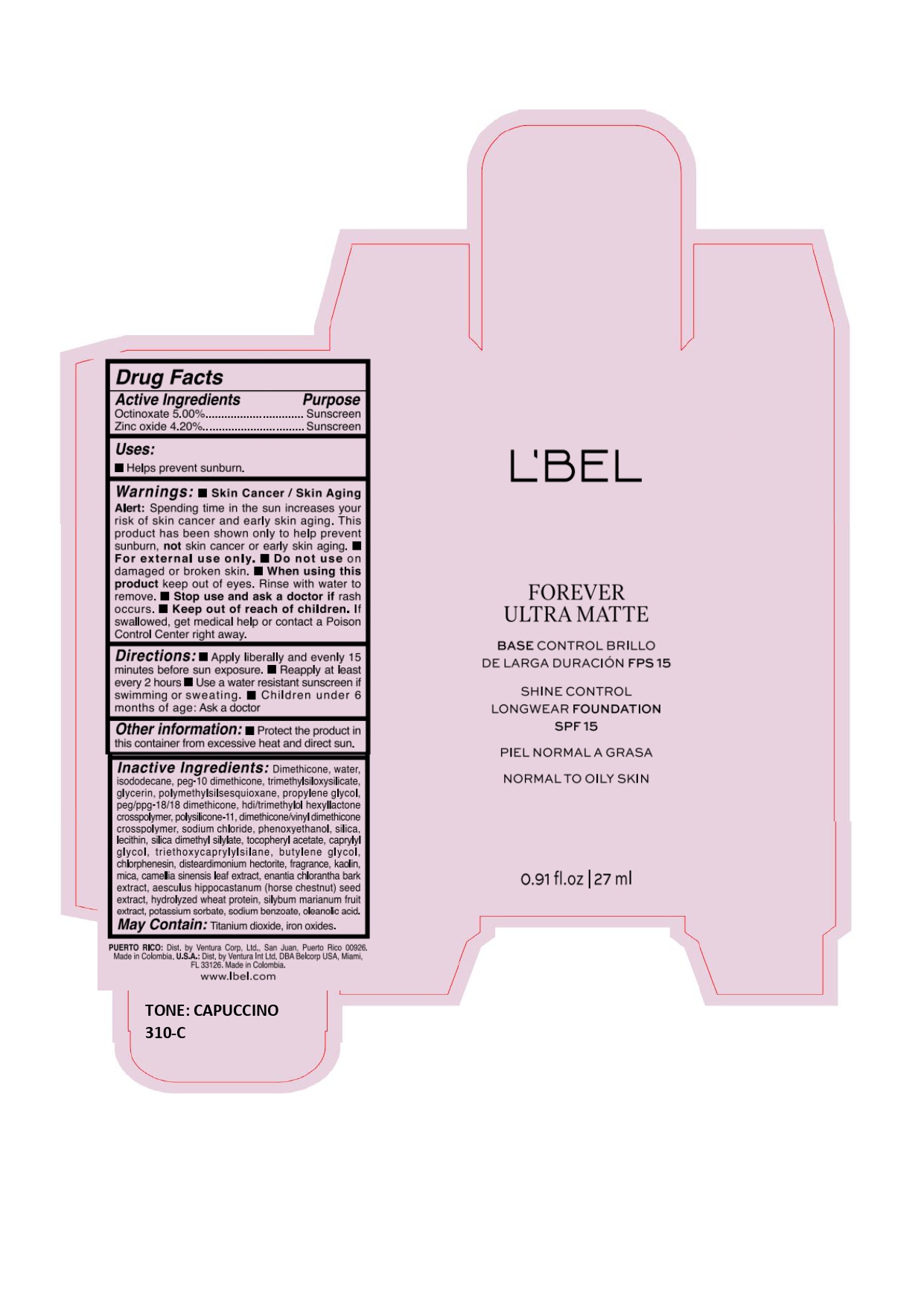 DRUG LABEL: LBEL FOREVER ULTRA MATTE BASE CONTROL BRILLO DE LARGA DURACION FPS 15 SHINE CONTROL LONGWEAR FOUNDATION SPF 15 LATTE 180-F
NDC: 14141-316 | Form: EMULSION
Manufacturer: Bel Star S.A.
Category: otc | Type: HUMAN OTC DRUG LABEL
Date: 20241028

ACTIVE INGREDIENTS: ZINC OXIDE 42 mg/1 mL; OCTINOXATE 50 mg/1 mL
INACTIVE INGREDIENTS: FERRIC OXIDE RED; FERROSOFERRIC OXIDE; .ALPHA.-TOCOPHEROL ACETATE; CAPRYLYL GLYCOL; HYDROLYZED WHEAT PROTEIN (ENZYMATIC, 3000 MW); PEG/PPG-18/18 DIMETHICONE; SILICON DIOXIDE; TRIETHOXYCAPRYLYLSILANE; MICA; ANNICKIA CHLORANTHA BARK; MILK THISTLE; KAOLIN; WATER; POLYMETHYLSILSESQUIOXANE (4.5 MICRONS); DIMETHICONE/VINYL DIMETHICONE CROSSPOLYMER (SOFT PARTICLE); POTASSIUM SORBATE; SODIUM BENZOATE; LECITHIN, SOYBEAN; TITANIUM DIOXIDE; FERRIC OXIDE YELLOW; PEG-10 DIMETHICONE (220 CST); TRIMETHYLSILOXYSILICATE (M/Q 0.6-0.8); HEXAMETHYLENE DIISOCYANATE/TRIMETHYLOL HEXYLLACTONE CROSSPOLYMER; SILICA DIMETHYL SILYLATE; GREEN TEA LEAF; BUTYLENE GLYCOL; CHLORPHENESIN; DISTEARDIMONIUM HECTORITE; ISODODECANE; DIMETHICONE; GLYCERIN; PROPYLENE GLYCOL; PHENOXYETHANOL; OLEANOLIC ACID; HORSE CHESTNUT; SODIUM CHLORIDE

L'BEL FOREVER ULTRA MATTE BASE CONTROL BRILLO DE LARGA DURACIÓN FPS 15 SHINE CONTROL LONGWEAR FOUNDATION SPF 15

Active Ingredients

Octinoxate 5.00%

Zinc oxide 4.20%

Purpose

Sunscreen

Uses

- Helps prevent sunburn.

Warnings

- Skin Cancer/Skin Aging Alert: Spending time in the sun increases your risk of skin cancer and early skin aging. This product has been shown only to help prevent sunburn, not skin cancer or early skin aging.
- For external use only.

Do not use

on damaged or broken skin.

When using this product

keep out of eyes. Rinse with water to remove.

Stop use and ask a doctor if

rash occurs.

Keep out of reach of children.

If swallowed, get medical help or contact a Poison Control Center right away.

Directions

- Apply liberally and evenly 15 minutes before sun exposure.
- Reapply at least every 2 hours
- Use a water resistant sunscreen if swimming or sweating.
- Children under 6 months of age: Ask a doctor

Other information

- Protect the product in this container from excessive heat and direct sun.

Inactive Ingredients

Dimethicone, water, isododecane, peg-10 dimethicone, trimethylsiloxysilicate, glycerin, polymethylsilsesquioxane, propylene glycol, peg/ppg-18/18 dimethicone, hdi/trimethylol hexyllactone crosspolymer, polysilicone-11, dimethicone/vinyl dimethicone crosspolymer, sodium chloride, phenoxyethanol, silica, lecithin, silica dimethyl silylate, tocopheryl acetate, caprylyl glycol, triethoxycaprylylsilane, butylene glycol, chlorphenesin, disteardimonium hectorite, fragrance, kaolin, mica, camellia sinensis leaf extract, enantia chlorantha bark extract, aesculus hippocastanum (horse chestnut) seed extract, hydrolyzed wheat protein, silybum marianum fruit extract, potassium sorbate, sodium benzoate, oleanolic acid.

May Contain :

Titanium dioxide, iron oxides.

Company information

PUERTO RICO: Dist. by Ventura Corp, Ltd., San Juan, Puerto Rico 00926.

USA: Dist. by Ventura Int Ltd. DBA Belcorp USA, Miami, FL 33126.

Made in Colombia.

www.lbel.com